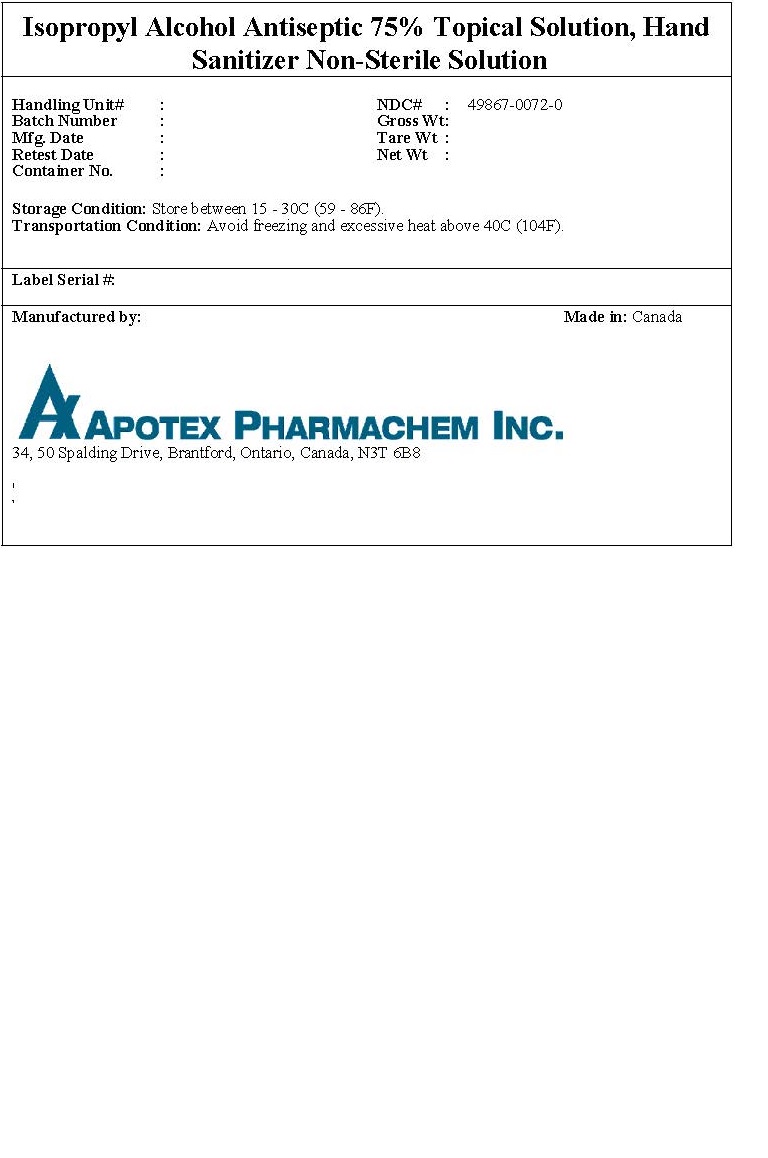 DRUG LABEL: Isopropyl Alcohol
NDC: 49867-0072 | Form: SOLUTION
Manufacturer: Apotex Pharmachem Inc.
Category: otc | Type: HUMAN OTC DRUG LABEL
Date: 20200413

ACTIVE INGREDIENTS: Isopropyl Alcohol 750 g/1 kg
INACTIVE INGREDIENTS: Glycerin; Hydrogen Peroxide; Water

Drug Facts

Active ingredient(s)

Isopropyl Alcohol Antiseptic 75% Topical Solution, Hand Sanitizer Non-Sterile Solution

Purpose

Antiseptic

Use(s)

Hand sanitizer to help reduce bacteria that potentially can cause disease. For use when soap and water are not available.

Warnings

For external use only. Keep away from open flame and sources of heat.

Do not use on children less than 2 months old.

Do not use on open skin wounds.

Ask a doctor before use if

Information required in 201.66(c)(5)(iv)

Ask a doctor or pharmacist before use if

Information required in 201.66(c)(5)(v)

When using this product keep out of eyes, ears and mouth. In case of contact with eyes, rinse eyes thoroughly with water

Stop use and ask doctor if

Stop use and ask a doctor if irritation or rash occurs. These may be signs of a serious condition.

Other required warnings

Information required in 201.66 (c)(5)(viii)

Pregnancy/Breastfeeding

Information required in 201.66(c)(5)(ix)

Keep out of reach of children, if swallowed, call a poison control center right away.

Directions

Place enough product on hands to cover all surfaces. Rub hands together until dry. Supervise children under 6 years of age when using this product to avoid swallowing.

Other information

Store between 15-30C (59-86F) Avoid freezing and excessive heat above 40C (104F)

Storage

Store between 15-30C (59-86F) Avoid freezing and excessive heat above 40C (104F)

Inactive ingredients

glycerin, hydrogen peroxide, water

Questions

Questions? 1-800-667-4708 or 1-416-401-7780 (follow prompts)

Report adverse reactions to the above numbers or drugsafety@apotex.com

Principal Display Panel

Representative sample of labeling: PRINCIPAL DISPLAY PANEL - DRUM LABEL ISOPROPYL ALCOHOL ANTISEPTIC 75% TOPICAL SOLUTION, HAND SANITIZER NON-STERILE SOLUTION: HANDLING UNIT #: NDC 49867-0072-0: BATCH NUMBER.: GROSS WT.: MFG. DATE: TARE WT.: RETEST DATE: NET WT.: CONTAINER NO.: STORAGE CONDITION: STORE BETWEEN 15-30C (59-86F): TRANSPORTATION CONDITION: AVOID FREEZING AND EXCESSIVE HEAT ABOUVE 40C (104F): LABEL SERIAL #: MANUFACTURED BY APOTEX PHARMACHEM INC.: MADE IN: CANADA